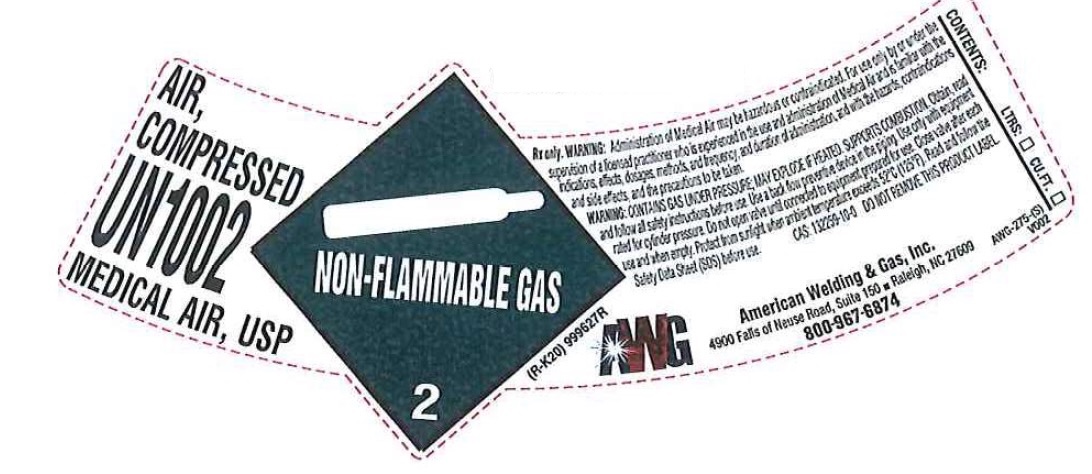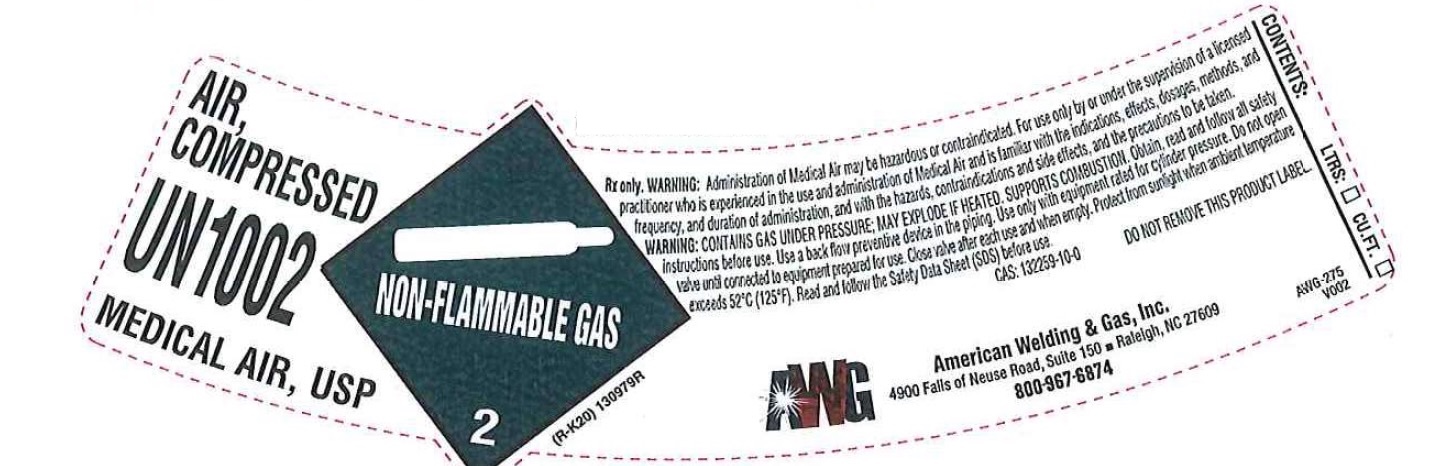 DRUG LABEL: Air
NDC: 44076-020 | Form: GAS
Manufacturer: American Welding & Gas, Inc.
Category: prescription | Type: HUMAN PRESCRIPTION DRUG LABEL
Date: 20251216

ACTIVE INGREDIENTS: AIR 1000 mL/1 L

Air

PACKAGE LABEL

AIR, COMPRESSED – MEDICAL AIR, USP – UN1002

Rx only. WARNING:
Administration of Medical Air may be hazardous or contraindicated. For use only by or under the supervision of a licensed practitioner who is experienced in the use and administration of Medical Air and is familiar with the indications, effects, dosages, methods, frequency, and duration of administration, and with the hazards, contraindications and side effects, and the precautions to be taken. WARNING: CONTAINS GAS UNDER PRESSURE, MAY EXPLODE IF HEATED. SUPPORTS COMBUSTION. Obtain, read, and follow all safety instructions before use. Use a back flow preventive device in the piping. Use only with equipment rated for cylinder pressure. Do not open valve until connected to equipment prepared for use. Close valve after each use and when empty. Protect from sunlight when ambient temperature exceeds 52C (125F). Read and follow the Safety Data Sheet (SDS) before use.

CAS: 132259-10-0
DO NOT REMOVE THIS PRODUCT LABEL

American Welding & Gas, Inc.
4900 Falls of Neuse Road, Suite 150
Raleigh, NC 27609
800-967-6874

CONTENTS:
LITERS CU.FT.